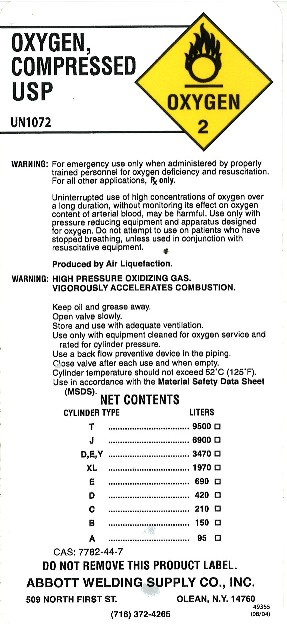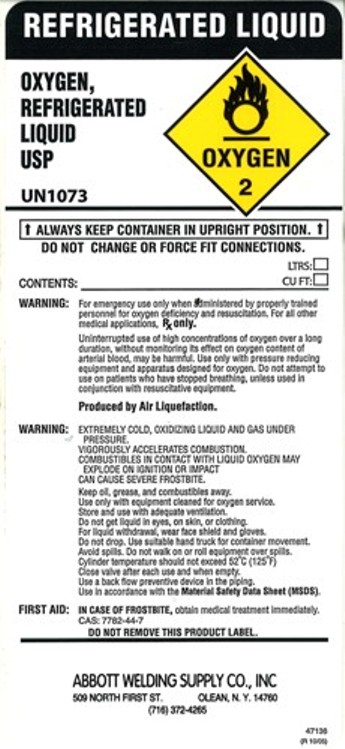 DRUG LABEL: Oxygen
NDC: 49317-001 | Form: GAS
Manufacturer: Abbott Welding Supply
Category: prescription | Type: HUMAN PRESCRIPTION DRUG LABEL
Date: 20110816

ACTIVE INGREDIENTS: Oxygen 995 mL/1 L

Oxygen Compressed Label

PACKAGE LABEL

Oxygen, compressed usp
Oxygen 2
UN1072
Warning: For emergency use only when administered by properly trained personnel for oxygen deficiency and resuscitation. For all other applications Rx only.
Uninterrupted use of high concentrations of oxygen over a long duration, without monitoring its effect on oxygen content of arterial blood, may be harmful. Use only with pressure reducing equipment and apparatus designed for oxygen. Do not attempt to use on patients who have stopped breathing, unless used in conjunction with resuscitative equipment.
Produced by Air Liquefaction.
Warning: High Pressure Oxidizing Gas.
Vigorously accelerates combustion.
Keep oil and grease away.
Open valve slowly.
Store and use with adequate ventilation.
Use only with equipment cleaned for oxygen service and rated for cylinder pressure.
Use a back flow preventive device in the piping.
Close valve after each use and when empty.
Cylinder temperature should not exceed 52 degrees Celsius (125 degrees Fahrenheit).
Use in accordance with the material safety data sheet(MSDS).

Net Contents

Cylinder Type Liters
T 9500
J 6900
D,E,Y 3470
XL 1970
E 690
D 420
C 210
B 150
A 95

CAS:7782-44-7

Do not remove this product label.
Abbott Welding Supply Co., Inc.
509 North First St. Olean, N.Y. 14760
(716)372-4265

49335 (08/04)

PACKAGE LABEL

Oxygen, Refrigerated Liquid
USP
Oxygen 2
UN1073
Always keep container in upright position.
Do not change or force fit connections.
Contents: ltrs. cu ft.
Warning: For emergency use only when administered by properly trained personnel for oxygen deficiency and resuscitation. For all other applications Rx only.
Uninterrupted use of high concentrations of oxygen over a long duration, without monitoring its effect on oxygen content of arterial blood, may be harmful. Use only with pressure reducing equipment and apparatus designed for oxygen. Do not attempt to use on patients who have stopped breathing, unless used in conjunction with resuscitative equipment.
Produced by Air Liquefaction.
Warning: Extremely cold oxidizing liquid and gas under pressure.
Vigorously accelerates combustion.
Combustibles in contact with liquid oxygen may explode on ignition or impact
Can cause severe frostbite.
Keep oil, grease and combustibles away.
Use only with equipment cleaned for oxygen service.
Store and use with adequate ventilation.
Do not get liquid in eyes, on skin, or clothing.
For liquid withdrawal, wear face shield and gloves.
Do not drop. Use suitable hand truck for container movement.
Avoid spills. Do not walk on or roll equipment over spills.
Cylinder temperature should not exceed 52 degrees Celsius (125 degrees Fahrenheit).
Close valve after each use and when empty.
Use a back flow preventive device in the piping.
Use in accordance with the material safety data sheet(MSDS).
First Aid: In case of frostbite, obtain medical treatment immediately.
CAS:7782-44-7
Do not remove this product label.
Abbott Welding Supply Co., Inc.
509 North First St. Olean, N.Y. 14760
(716)372-4265
47136 (R 10/05)